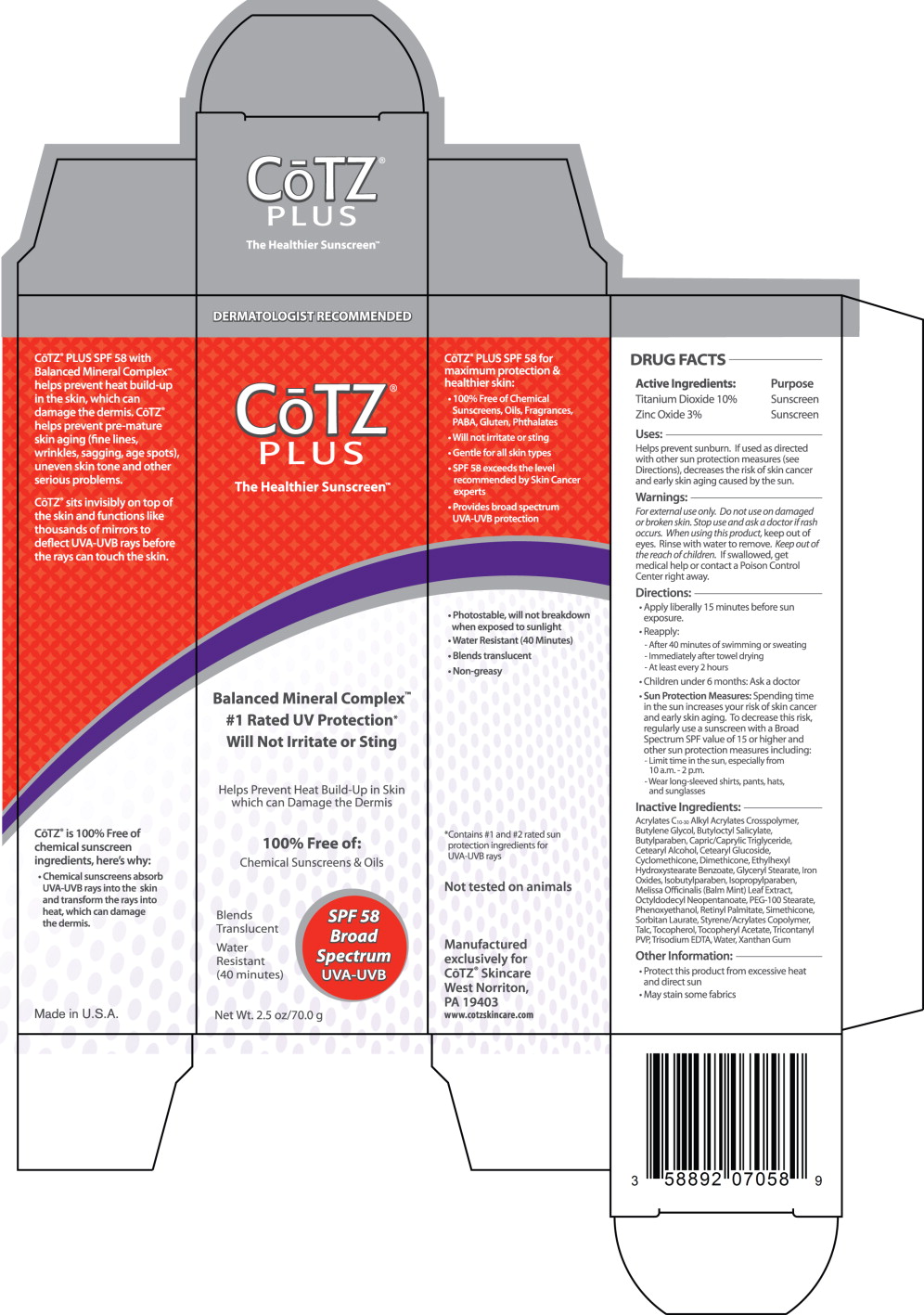 DRUG LABEL: Cotz Plus SPF 58 
NDC: 58892-070 | Form: CREAM
Manufacturer: Fallien Cosmeceuticals, LTD.
Category: otc | Type: HUMAN OTC DRUG LABEL
Date: 20130102

ACTIVE INGREDIENTS: Titanium Dioxide 100 mg/1 g; Zinc Oxide 30 mg/1 g
INACTIVE INGREDIENTS: Butylene Glycol; Butylparaben; Medium-Chain Triglycerides; Carbomer Copolymer Type B (Allyl Pentaerythritol Crosslinked); Cetostearyl Alcohol; Cetearyl Glucoside; Cyclomethicone; Dimethicone; Edetate Trisodium; Glyceryl Monostearate; Ferric Oxide Yellow; Ferrosoferric Oxide; Isobutylparaben; Isopropylparaben; Melissa Officinalis Leaf; Octyldodecyl Neopentanoate; PEG-100 Stearate; Phenoxyethanol; Vitamin A Palmitate; Sorbitan Monolaurate; Talc; Tocopherol; .Alpha.-Tocopherol Acetate; Tricontanyl Povidone (4 Tricontanyl Branches/Repeat); Water; Xanthan Gum

DRUG FACTS

Active Ingredients:

Titanium Dioxide 10%

Zinc Oxide 3%

Purpose

Sunscreen

Sunscreen

Uses:

Helps prevent sunburn. If used as directed with other sun protection measures (see Directions), decreases the risk of skin cancer and early skin aging caused by the sun.

Warnings:

For external use only.

Do not use on damaged or broken skin.

Stop use and ask a doctor if rash occurs.

When using this product, keep out of eyes. Rinse with water to remove.

KEEP OUT OF REACH OF CHILDREN

Keep out of the reach of children. If swallowed, get medical help or contact a Poison Control Center right away.

Directions:

- Apply liberally 15 minutes before sun exposure.
- Reapply:
  - After 40 minutes of swimming or sweating
  - Immediately after towel drying
  - At least every 2 hours
- Children under 6 months: Ask a doctor
- Sun Protection Measures: Spending time in the sun increases your risk of skin cancer and early skin aging. To decrease this risk, regularly use a sunscreen with a Broad Spectrum SPF value of 15 or higher and other sun protection measures including:
  - Limit time in the sun, especially from 10 a.m.-2 p.m.
  - Wear long-sleeved shirts, pants, hats, and sunglasses

Inactive Ingredients:

Acrylates C10-30 Alkyl Acrylates Crosspolymer, Butylene Glycol, Butyloctyl Salicylate, Butylparaben, Capric/Caprylic Triglyceride, Cetearyl Alcohol, Cetearyl Glucoside, Cyclomethicone, Dimethicone, Ethylhexyl Hydroxystearate Benzoate, Glyceryl Stearate, Iron Oxides, Isobutylparaben, Isopropylparaben, Melissa Officinalis (Balm Mint) Leaf Extract, Octyldodecyl Neopentanoate, PEG-100 Stearate, Phenoxyethanol, Retinyl Palmitate, Simethicone, Sorbitan Laurate, Styrene/Acrylates Copolymer, Talc, Tocopherol, Tocopheryl Acetate, Tricontanyl PVP, Trisodium EDTA, Water, Xanthan Gum

Other Information:

- Protect this product from excessive heat and direct sun
- May stain some fabrics

Principal Display Panel – 2.5 oz Carton Label

DERMATOLOGIST RECOMMENDED

CoTZ®

PLUS

The Healthier Sunscreen TM

Balanced Mineral Complex™

#1 Rated UV Protection*

Will Not Irritate or Sting

Helps Prevent Heat Build-Up in Skin
which can Damage the Dermis

100% Free of:

Chemical Sunscreens & Oils

SPF 58 Broad

Spectrum

UVA-UVB

Blends
Translucent

Water
Resistant
(40 minutes)

Net Wt. 2.5 oz/70.0 g